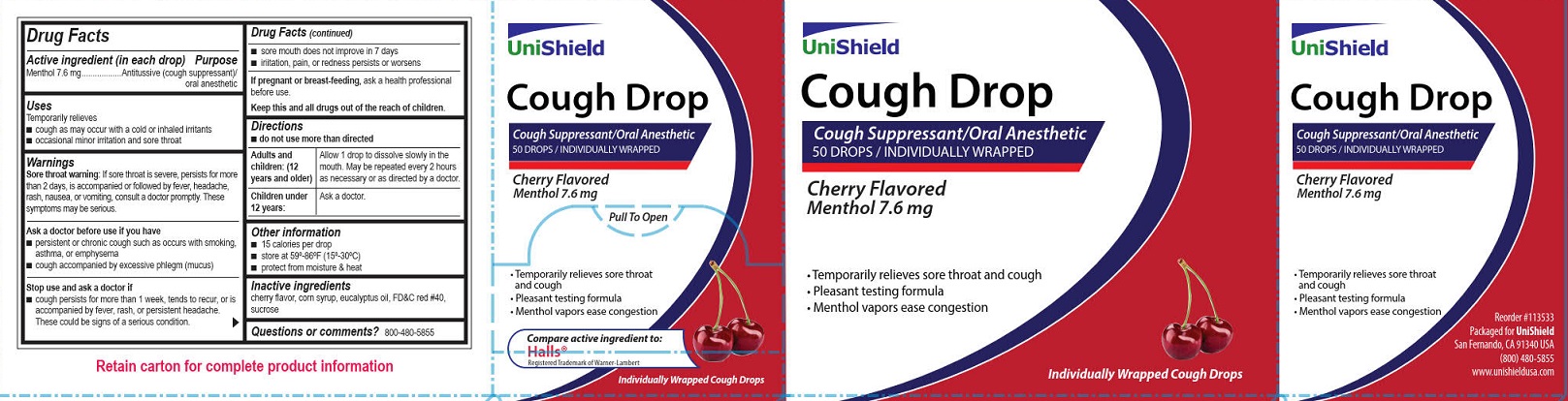 DRUG LABEL: Unishield Cherry Cough
NDC: 49314-0505 | Form: LOZENGE
Manufacturer: Unishield
Category: otc | Type: HUMAN OTC DRUG LABEL
Date: 20250909

ACTIVE INGREDIENTS: MENTHOL, UNSPECIFIED FORM 7.6 mg/1 1
INACTIVE INGREDIENTS: EUCALYPTUS OIL; CORN SYRUP; FD&C RED NO. 40; SUCROSE

Unishield Cherry Cough Drops

Drug Facts

Active ingredient (in each drop)

Menthol 7.6 mg

Purpose

Antitussive (cough suppressant)/oral anesthetic

Uses

Temporarily relieves

- cough as may occur with a cold or inhaled irritants
- occasional minor irritation and sore throat

Warnings

Sore throat warning: If sore throat is severe, persists for more
than 2 days, is accompanied or followed by fever, headache,
rash, nausea, or vomiting, consult a doctor promptly. These
symptoms may be serious.

Ask a doctor before use

- persistent or chronic cough such as occurs with smoking, asthma, or emphysema
- cough accompanied by excessive phlegm (mucus)

Stop use and ask a doctor if

- cough persists for more than 1 week, tends to recur, or is accompanied by fever, rash, or persistent headache. These could be signs of a serious condition.
- sore mouth does not improve in 7 days
- irritation, pain, or redness persists or worsens

PREGNANCY OR BREAST FEEDING

If pregnant or breast-feeding, ask a health professional before use.

KEEP OUT OF REACH OF CHILDREN

Keep this and all drugs out of the reach of children.

Directions

- do not use more than directed

Adults and children: (12 years and older)

Allow 1 drop to dissolve slowly in the mouth. May be repeated every 2 hours as necessary or as directed by a doctor.

Children under 12 years:

Ask a doctor

Other information

- 15 calories per drop
- store at 59º-86ºF (15º-30ºC)
- protect from moisture & heat

Inactive ingredients:

cherry flavor, corn syrup, eucalyptus oil, FD&C red #40, sucrose

Questions or comments? 800-480-5855

PACKAGE LABEL

Unishield

Cough Drop

Cough Suppressant/Oral Anesthetic

50 Drops/Individually Wrapped

Cherry Flavored

Menthol 7.6 mg

Pull To Open

• Temporarily relieves sore throat and cough

• Pleasant tasting formula

• Menthol vapors ease congestion

Compare active ingredients to:

Hall®

Registered Trademark of Warner-Lambert

Individually Wrapped Cough Drops